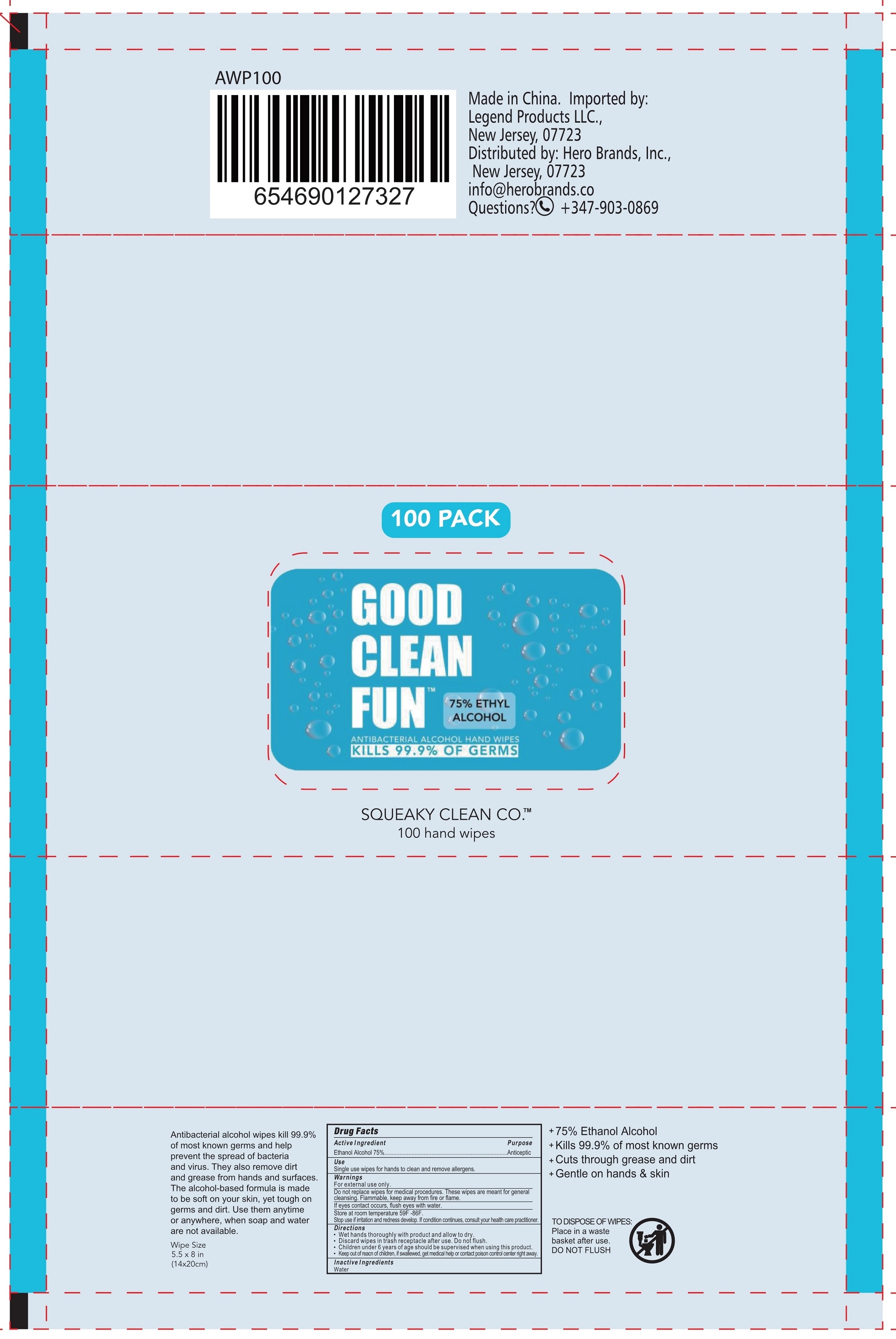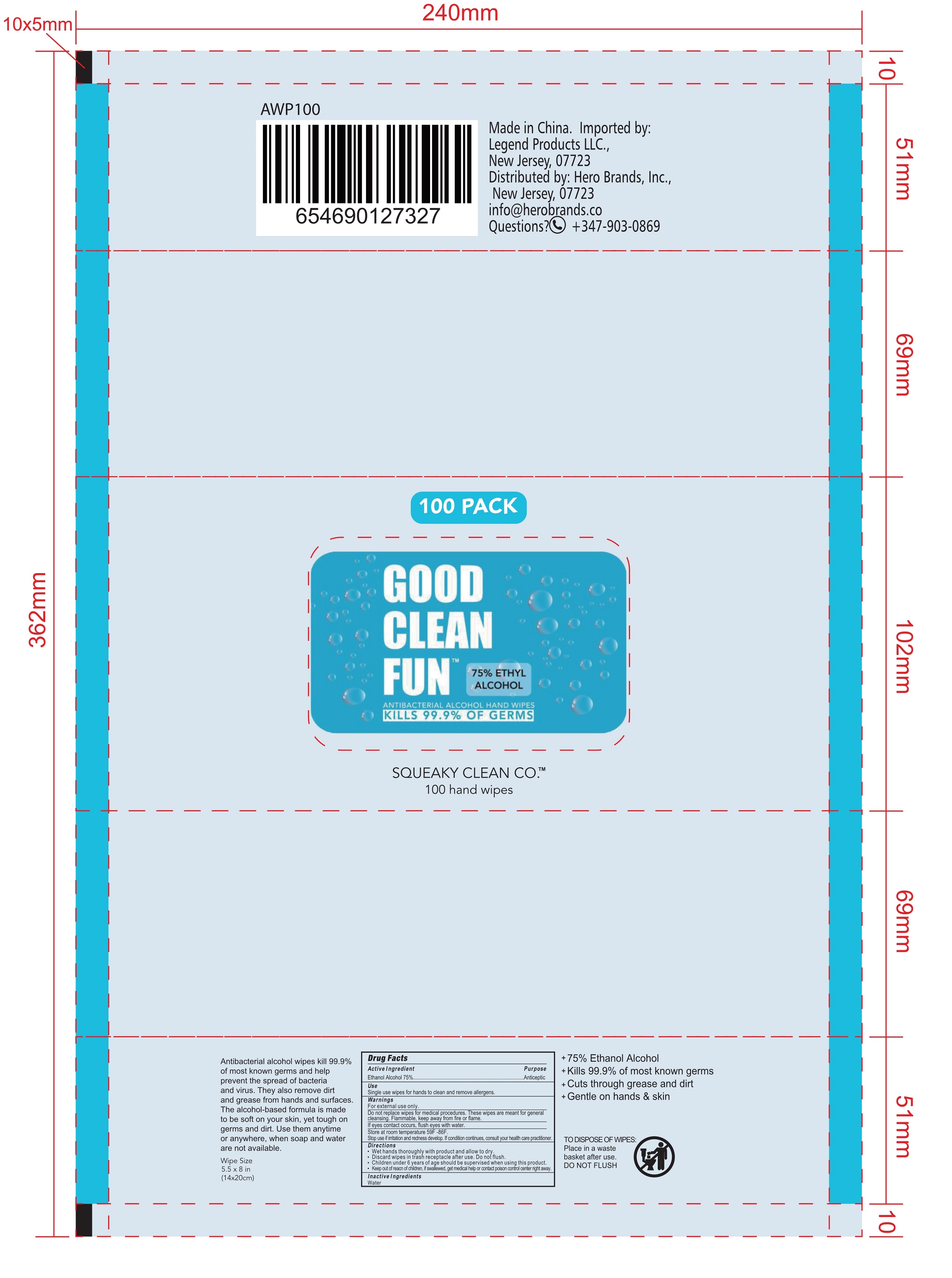 DRUG LABEL: ANTIBACTERIAL ALCOHOL HAND WIPES
NDC: 75163-108 | Form: CLOTH
Manufacturer: Zhuji Jianhe Paper Co., Ltd
Category: otc | Type: HUMAN OTC DRUG LABEL
Date: 20200729

ACTIVE INGREDIENTS: ALCOHOL 3.5 mL/1 1
INACTIVE INGREDIENTS: WATER

75163-108 zhuji jianhe 100pack

Active Ingredient(s)

Alcohol 75% v/v. Purpose: Antiseptic

Inactive ingredients

Water

Purpose

Daily Clean for daily items and Antimicrobial.

WHEN USING

This product is used to wipe hands, faces, skins, etc. It can also be used to clean many kinds of places.

Do not use

on children less than 2 months of age
on open skin wounds

STOP USE

if irritation or rash occurs.

These may be signs of a serious condition.

Keep out of reach of children.

Use

Single use wipes for hands to clean and remove allergens.

Directions

Wet hands thoroughly with product and allow to dry.
Discard wipes in trash receptacle after use. Do not flush.
Children under 6 years of age should be supervised when using this product.
Keep out of reacn of children, if swallewed, get medical help or contact poison control center right away.

Warnings

For external use only.
Do not replace wipes for medical procedures. These wipes are meant for general
cleansing. Flammable, keep away from fire or flame.
If eyes contact occurs, flush eyes with water.
Store at room temperature 59F -86F.
Stop use if irritation and redness develop. If condition continues, consult your health care practitioner.

Other information

- Store at room temperature 59F -86F.

Package label. Principal display panel

100 CLOTH in 1 BAG ,NDC:75163-108-01